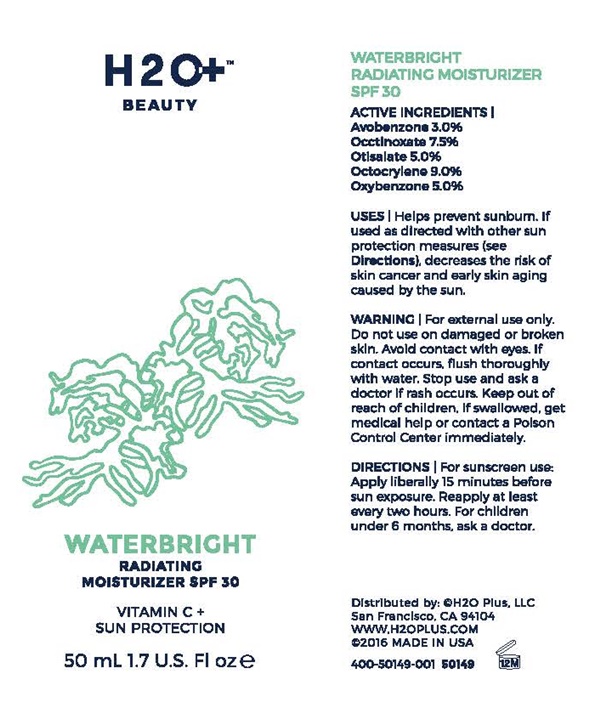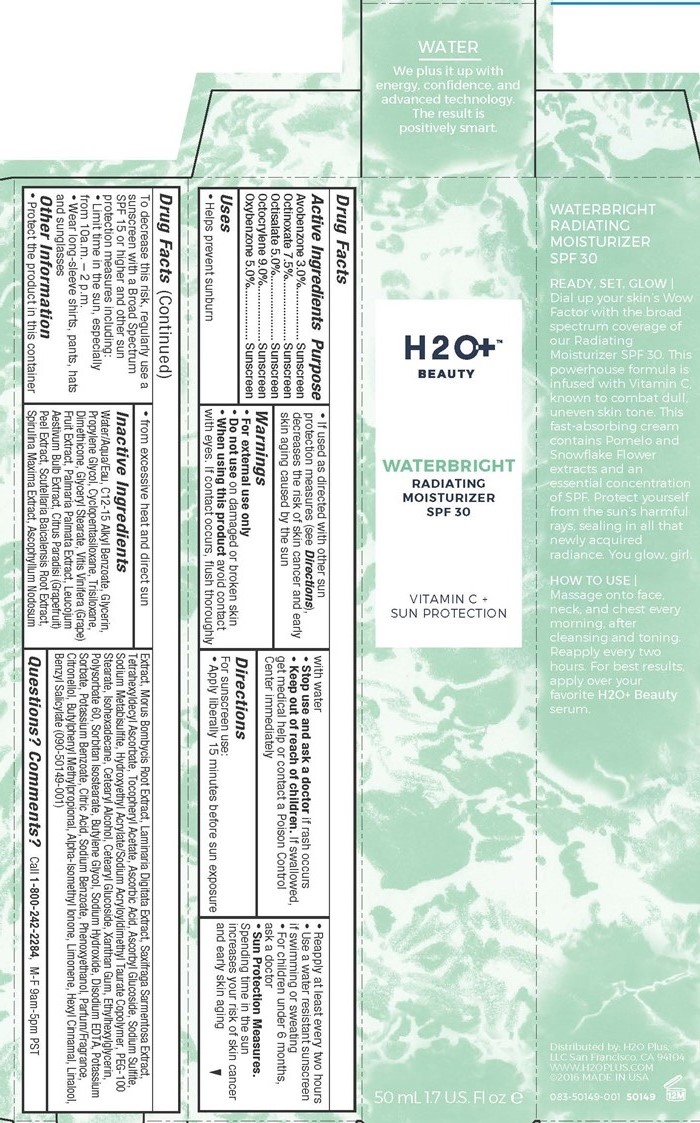 DRUG LABEL: WATERBRIGHT RADIATING
NDC: 54111-129 | Form: CREAM
Manufacturer: Bentley Laboratories, LLC
Category: otc | Type: HUMAN OTC DRUG LABEL
Date: 20181219

ACTIVE INGREDIENTS: AVOBENZONE 1.5 g/50 mL; OCTINOXATE 3.75 g/50 mL; OCTISALATE 2.5 g/50 mL; OCTOCRYLENE 4.5 g/50 mL; OXYBENZONE 2.5 g/50 mL
INACTIVE INGREDIENTS: WATER; ALKYL (C12-15) BENZOATE; GLYCERIN; PROPYLENE GLYCOL; CYCLOMETHICONE 5; TRISILOXANE; DIMETHICONE; GLYCERYL MONOSTEARATE; WINE GRAPE; DULSE; LEUCOJUM AESTIVUM BULB; GRAPEFRUIT PEEL; SCUTELLARIA BAICALENSIS ROOT; SPIRULINA MAXIMA; ASCOPHYLLUM NODOSUM; MORUS AUSTRALIS ROOT; LAMINARIA DIGITATA; SAXIFRAGA STOLONIFERA LEAF; TETRAHEXYLDECYL ASCORBATE; .ALPHA.-TOCOPHEROL ACETATE; ASCORBIC ACID; ASCORBYL GLUCOSIDE; SODIUM SULFITE; SODIUM METABISULFITE; HYDROXYETHYL ACRYLATE/SODIUM ACRYLOYLDIMETHYL TAURATE COPOLYMER (100000 MPA.S AT 1.5%); PEG-100 STEARATE; ISOHEXADECANE; CETOSTEARYL ALCOHOL; CETEARYL GLUCOSIDE; XANTHAN GUM; ETHYLHEXYLGLYCERIN; POLYSORBATE 60; SORBITAN ISOSTEARATE; BUTYLENE GLYCOL; SODIUM HYDROXIDE; EDETATE DISODIUM; POTASSIUM SORBATE; POTASSIUM BENZOATE; CITRIC ACID MONOHYDRATE; SODIUM BENZOATE; PHENOXYETHANOL; .BETA.-CITRONELLOL, (+/-)-; BUTYLPHENYL METHYLPROPIONAL; ISOMETHYL-.ALPHA.-IONONE; LIMONENE, (+)-; BENZYL SALICYLATE

Waterbright Radiating - 129

Drug Facts Active Ingredients

Avobenzone 3.0%

Octinoxare 7.5%

Octisalate 5.0%

Octocrylene 9.0%

Oxybenzone 5.0%

Purpose

Sunscreen

Keep out of reach of children

If swallowed, get medical help or contact a Poison Control Center immediately.

Uses

- Helps prevent sunburn
- If used as directed with other sun protection measures (see Directions), decreases the risk of skin cancer and early skin aging caused by the sun

Warnings

- For external use only

Do not use

on damaged or broken skin

When using this product

avoid contact with eyes. If contact occurs, flush thoroughly with water

Stop use and ask a doctor

if rash occurs

Directions

For sunscreen use:

- Apply liberally 15 minutes before sun exposure
- Reapply at least every two hours
- Use a water resistant sunscreen if swimming or sweating
- For children under 6 months, ask a doctor

- Sun Protection Measures.

Spending time in the sun increases your risk of skin cancer and early skin aging.

To decrease this risk, regularly use a sunscreen with a Broad Spectrum SPF 15 or higher and other sun protection measures including:

- Limit time in the sun, especially from 10 a.m. - 2 p.m.
- Wear long-sleeve shirts, pants, hats and sunglasses

Other Information

- Protect the product in this container

- from excessive heat and direct sun

Inactive Ingredients

Water/Aqua/Eau, C12-15 Alkyl Benzoate, Glycerin, Propylene Glycol, Cyclopentasiloxane, Trisiloxane, Dimethicone, Glyceryl Stearate, Vits Vinifera (Grape) Fruit Extract, Palmaria, Palmata Extract, Leucojum Aestivum Bulb Extract, Citrus Paradis (Grapefruit) Peel Extract, Scutellaria Balcalensis Root Extract, Spirulina Maxima Extract, Ascophyllum Nodosum Extract, Morus Bombycic Root Extract, Laminaria Digitala Extract, Saxifraga Sarmentosa Extract, Tetrahexyldecyl Ascorbate, Tocopheryl Acetate, Ascorbic Acid, Ascorbyl Glucoside, Sodium Sulfite, Sodium Metabisulfite, Hydroxyethyl Acrylate/Sodium Acryloyldimethyl Taurate Copolymer, PEG-100 Stearate, Isohexadecane, Cetearyl Alcohol, Cetearyl Glucoside, Xanthan Gum, Ethylhexylglycerin, Polysorbate 60, Sorbitan Isostearate, Butylene Glycol, Sodium Hydroxide, Disodium EDTA, Potassium Sorbate, Potassium Benzoate, Citric Acid, Sodium Benzoate, Phenoxyethanol, Parfum/Fragrance, Citronellol, Butylphenyl Methylpropional, Alpha-Isomethyl Ionone, Limonene, Hexyl Cinnamal, Linalool, Benzyl Salicylate (090-50149-001)

Questions? Comments?

Call 1-800-242-2284, M-F 9am-5pm PST

H2O BEAUTY product label

H2O+ ™

BEAUTY

WATERBRIGHT
RADIATING MOISTURIZER
SPF 30

VITAMIN C + SUN PROTECTION

50 mL 1.7 U.S. Fl oz

WATER

We plus it up with energy, confidence, and advanced technology. The result is positively smart.

WATERBRIGHT RADIATING MOISTURIZER SPF 30

READY. SET. GLOW!

Dial up your skin's Wow Factor with the broad spectrum coverage of our Radiating Moisturizer SPF 30. This powerhouse formula is infused with Vitamin C known to combat dull, uneven skin tone. This fast absorbing cream contains Pomelo and Snowflake Flower extracts and an essential concentration of SPF. Protect yourself from the sun's harmful rays, sealing in all that newly acquired radiance. You glow, girl.

HOW TO USE
Massage on to face, neck, and chest every morning after cleansing and toning. Reapply every two hours. For bestesults, apply over your favorite H2O+ Beauty serum.

Distributed by: H2O Plus, LLC

San Francisco, CA 94104

WWW.H2OPLUS.COM

2016 MADE IN THE USA

400-5014-001 50149